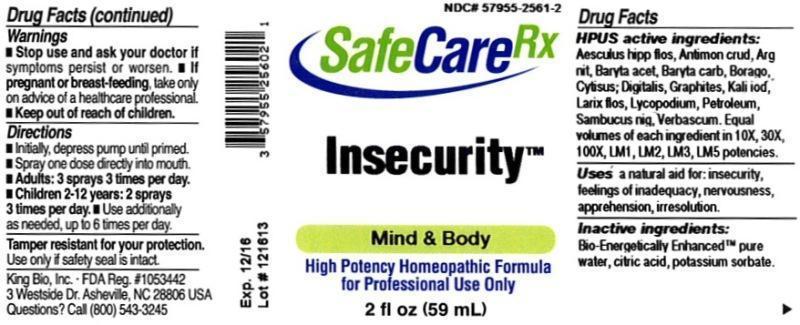 DRUG LABEL: Insecurity
NDC: 57955-2561 | Form: LIQUID
Manufacturer: King Bio Inc.
Category: homeopathic | Type: HUMAN OTC DRUG LABEL
Date: 20140109

ACTIVE INGREDIENTS: AESCULUS HIPPOCASTANUM FLOWER 10 [hp_X]/59 mL; ANTIMONY TRISULFIDE 10 [hp_X]/59 mL; SILVER NITRATE 10 [hp_X]/59 mL; BARIUM ACETATE 10 [hp_X]/59 mL; BARIUM CARBONATE 10 [hp_X]/59 mL; BORAGE 10 [hp_X]/59 mL; CYTISUS SCOPARIUS FLOWERING TOP 10 [hp_X]/59 mL; DIGITALIS 10 [hp_X]/59 mL; GRAPHITE 10 [hp_X]/59 mL; POTASSIUM IODIDE 10 [hp_X]/59 mL; LARIX DECIDUA FLOWERING TOP 10 [hp_X]/59 mL; LYCOPODIUM CLAVATUM SPORE 10 [hp_X]/59 mL; KEROSENE 10 [hp_X]/59 mL; SAMBUCUS NIGRA FLOWERING TOP 10 [hp_X]/59 mL; VERBASCUM THAPSUS 10 [hp_X]/59 mL
INACTIVE INGREDIENTS: WATER; CITRIC ACID MONOHYDRATE; POTASSIUM SORBATE

Insecurity™

ACTIVE INGREDIENT

HPUS active ingredients: Aesculus hippocastanum, flos, Antimonium crudum, Argentum nitricum, Baryta acetica, Baryta carbonica, Borago officinalis, Cytisus scoparius, Digitalis purpurea, Graphites, Kali iodatum, Larix decidua, flos, Lycopodium clavatum, Petroleum, Sambucus nigra, Verbascum thapsus. Equal volumes of each ingredient in 10X, 30X, 100X, LM1, LM2, LM3, LM5 potencies.

INDICATIONS AND USAGE

Uses a natural aid for: insecurity, feeling of inadequacy, nervousness, apprehension, irresolution.

INACTIVE INGREDIENT

Inactive Ingredients: Bio-Energetically Enhanced™ pure water, citric acid and potassium sorbate.

Warnings

- Stop use and ask a docter if symptoms persist or worsen.
- If pregnant or breast-feeding, take only on advice of a healthcare professional.

- Keep out of reach of children.

Directions

- Initially, depress pump until primed.
- Spray one dose directly into mouth.
- Adults: 3 sprays 3 times per day.
- Children 2-12 years: 2 sprays 3 times per day.
- Use additionally as needed, up to 6 times per day.

OTHER SAFETY INFORMATION

Tamper resistant for your protection. Use only if safety seal is intact.

PURPOSE

Uses a natural aid for:

- insecurity
- feelings of inadequacy
- nervousness
- apprehension
- irresolution